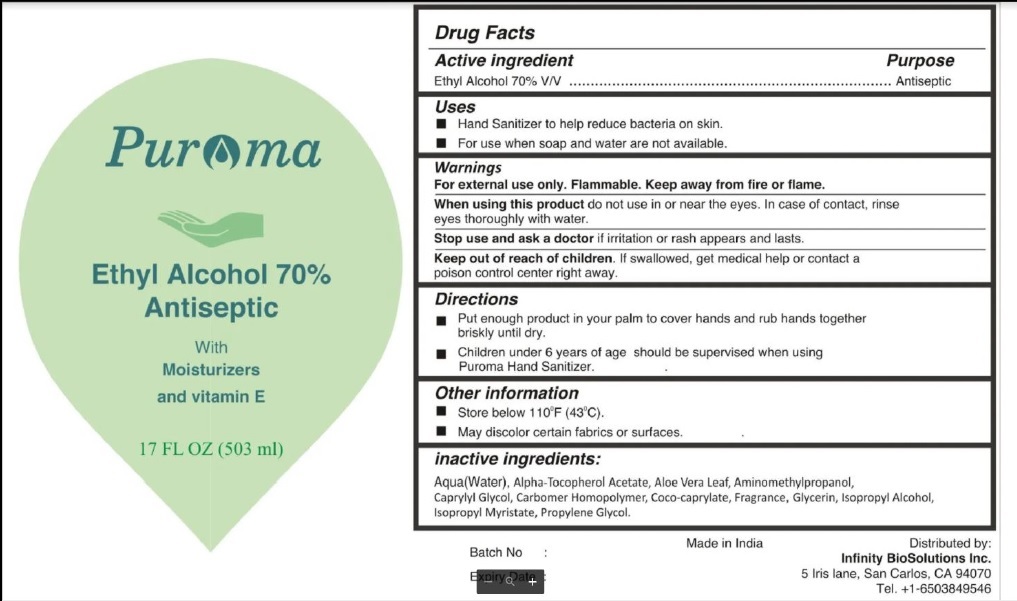 DRUG LABEL: PUROMA
NDC: 80948-002 | Form: GEL
Manufacturer: ZENITH MICRO CONTROL
Category: otc | Type: HUMAN OTC DRUG LABEL
Date: 20231213

ACTIVE INGREDIENTS: ALCOHOL 70 mL/100 mL
INACTIVE INGREDIENTS: WATER; ISOPROPYL ALCOHOL; GLYCERIN; ISOPROPYL MYRISTATE; .ALPHA.-TOCOPHEROL ACETATE; CARBOMER HOMOPOLYMER, UNSPECIFIED TYPE; CAPRYLYL GLYCOL; AMINOMETHYLPROPANOL; ALOE VERA LEAF; PROPYLENE GLYCOL; COCO-CAPRYLATE; FRAGRANCE CLEAN ORC0600327

PUROMA Ethyl Alcohol 70% Hand Sanitizer

Active Ingredient

Alcohol 70% V/V

Purpose

Antiseptic.

Warnings

- Flammable. Keep away from fire or flame.
- When using this product do not use in or near theeyes. In case of contact, rinse eyes thoroughly with water.
- Stop use and ask a doctor if irritation or rash appears and lasts.

Uses

Hand Sanitizer to help reduce bacteria on skin.

Directions

- Put enough product in your palm to cover hands and rub hands together briskly until dry.
- Children under 6 years of age should be supervised when using Puroma Hand Sanitizer.

Keep out of reach of children.

If swallowed, get medical help or contact a poison control center right away.

Other information

- Store below 110°F (430°C)
- May discolor certain fabrics or surfaces

Inactive Ingredients

WATER, ISOPROPYL ALCOHOL ,GLYCERIN, ISOPROPYL MYRISTATE,ALPHA.-TOCOPHEROL ACETATE, CARBOMER HOMOPOLYMER , CAPRYLYL GLYCOL,AMINOMETHYLPROPANOL, ALOE VERA LEAF, PROPYLENE GLYCOL,COCO-CAPRYLATE , FRAGRANCE.